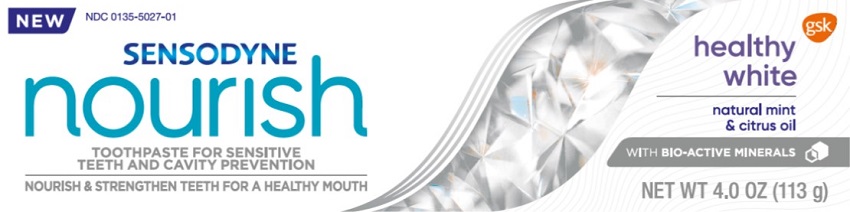 DRUG LABEL: Sensodyne

NDC: 0135-5027 | Form: PASTE
Manufacturer: Haleon US Holdings LLC
Category: otc | Type: HUMAN OTC DRUG LABEL
Date: 20240304

ACTIVE INGREDIENTS: POTASSIUM NITRATE 50 mg/1 g; SODIUM FLUORIDE 1.15 mg/1 g
INACTIVE INGREDIENTS: WATER; SORBITOL; HYDRATED SILICA; GLYCERIN; SODIUM LAURYL SULFATE; XANTHAN GUM; COCAMIDOPROPYL BETAINE; SACCHARIN SODIUM; TITANIUM DIOXIDE

Drug Facts

Active ingredients

Potassium nitrate 5%

Sodium fluoride 0.25% (0.15% w/v fluoride ion)

Purposes

Antihypersensitivity

Anticavity

Uses

- builds increasing protection against painful sensitivity of the teeth to cold, heat, acids, sweets, or contact.
- aids in the prevention of dental cavities.

Warnings

Stop use and ask a dentist if

- the problem persists or worsens. Sensitive teeth may indicate a serious problem that may need prompt care by a dentist.
- pain/sensitivity still persists after 4 weeks of use.

Keep out of reach of children.

If more than used for brushing is accidentally swallowed, get medical help or contact a Poison Control Center right away.

Directions

- adults and children 12 years of age and older:
  - apply at least a 1-inch strip of the product onto a soft bristle toothbrush.
  - brush teeth thoroughly for at least 1 minute twice a day (morning and evening), and not more than 3 times a day, or as recommended by a dentist or doctor. Make sure to brush all sensitive areas of the teeth. Minimize swallowing. Spit out after brushing.
- children under 12 years:Consult a dentist or doctor.

Other information

- do not store above 25°C (77°F)

Inactive ingredients

water, sorbitol, hydrated silica, glycerin, sodium lauryl sulfate, flavor, xanthan gum, cocamidopropyl betaine, sodium saccharin, titanium dioxide

Questions or comments?

1-866-844-2797

Additional Information

ALWAYS FOLLOW THE LABEL

SENSODYNE nourish

WITH BIO-ACTIVE MINERALS

- Brush twice daily for a healthier smile:
- Strengthens & nourishes teeth
- Effective & gentle whitening
- Helps prevent cavities
- Protects from sensitivity*
- Freshens breath

The Sensodyne Nourish rangewith bio-active minerals, strengthens and nourishes teeth while also protecting from sensitivity*. Our toothpaste is designed to provide the everyday nourishment your teeth to help protect the health of your mouth.

Healthy White:With trusted sensitivity protection*, our formulation, blended with natural mint and citrus oil, provides a fresh, cleansing sensation.

*with twice daily brush

Help us support the planet by recycling our packaging and being responsible with water usage.

Carton

Recycle

Tube

Recycle

Lot

See end of carton

Save Water

Turn off tap whilst brushing

Trademarks are owned by or licensed to the GSK group of companies.

©2021 GSK group of companies or its licensor.

Distributed by:

GSK Consumer Healthcare

Warren, NJ 07059

Principal Display Panel

NDC 0135-5027-01

NEW

SENSODYNE

nourish

TOOTHPASTE FOR SENSITIVE TEETH AND CAVITY PREVENTION

NOURISH & STRENGTHEN TEETH FOR A HEALTHY MOUTH

healthy white

natural mint & citrus oil

WITH BIO-ACTIVE MINERALS

NET WT 4.0 OZ (113 g)

62000000064837 Front Carton